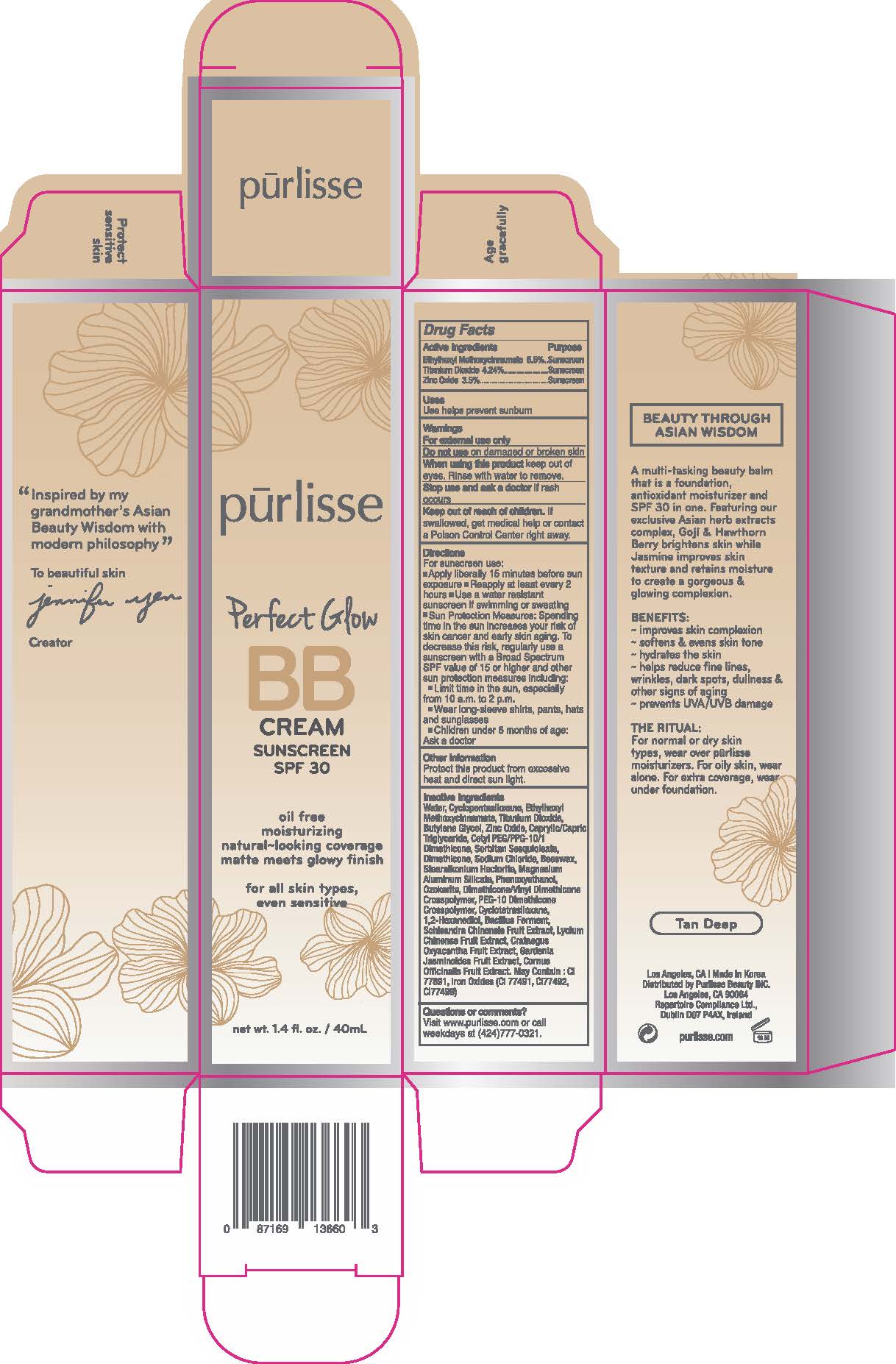 DRUG LABEL: Perfect Glow BB Cream Sunscreen SPF 30 - Tan Deep
NDC: 72407-418 | Form: CREAM
Manufacturer: Pur-lisse Beauty, LLC
Category: otc | Type: HUMAN OTC DRUG LABEL
Date: 20251230

ACTIVE INGREDIENTS: ZINC OXIDE 3.5 g/100 mL; TITANIUM DIOXIDE 4.3 g/100 mL; OCTINOXATE 6.5 g/100 mL
INACTIVE INGREDIENTS: SODIUM CHLORIDE; GARDENIA JASMINOIDES FRUIT; DIMETHICONE/VINYL DIMETHICONE CROSSPOLYMER (SOFT PARTICLE); WATER; FERROUS OXIDE; SORBITAN SESQUIOLEATE; LYCIUM CHINENSE FRUIT; MAGNESIUM ALUMINUM SILICATE; DIMETHICONE; CORNUS OFFICINALIS FRUIT; BEESWAX; 1,2-HEXANEDIOL; CYCLOTETRASILOXANE; CRATAEGUS LAEVIGATA FRUIT; PHENOXYETHANOL; PEG-10 DIMETHICONE (600 CST); CYCLOPENTASILOXANE; CAPRYLIC/CAPRIC TRIGLYCERIDE; CETYL PEG/PPG-10/1 DIMETHICONE (HLB 2); SCHISANDRA CHINENSIS FRUIT; STEARALKONIUM HECTORITE; BACILLUS POLYFERMENTICUS; CERESIN; BUTYLENE GLYCOL

Drug Facts

Active Ingredients

Octinoxate 6.5%

Titanium Dioxide 4.3%

Zinc Oxide 3.5%

Purpose

Sunscreen

Uses

Use helps prevent sunburn

Warnings

For external use only

Do not use on damaged or broken skin

When using this product keep out of eyes. Rinse with water to remove.

Stop use and ask a doctor if rash occurs

Keep out of reach of children. If swallowed, get medical help or contact a Poison Control Center right away.

Directions

For sunscreen use:

- Apply liberally 15 minutes before sun exposure
- Reapply at least every 2 hours
- Use a water resistant sunscreen if swimming or sweating
- Sun Protection Measures: Spending time in the sun increases your risk of skin cancer and early skin aging. To decrease this risk, regularly use a sunscreen with a Broad Spectrum SPF value of 15 or higher and other sun protection measures including:
- Limit time in the sun, especially from 10 a.m. to 2 p.m.
- Wear long-sleeve shirts, pants, hats and sunglasses
- Children under 6 months of age: Ask a doctor

Other Information

Protect this product from excessive heat and direct sun light.

Inactive Ingredients

Water, Cyclopentasiloxane, Butylene Glycol, Caprylic/Capric Triglyceride, Cetyl PEG/PPG-10/1 Dimethicone, Sorbitan Sesquioleate, Dimethicone, Sodium Chloride, Beeswax, Stearalkonium Hectorite, Magnesium Aluminum Silicate, Phenoxyethanol, Ozokerite, Dimethicone/Vinyl Dimethicone Crosspolymer, PEG-10 Dimethicone Crosspolymer, Cyclotetrasiloxane, 1,2-Hexanediol, Bacillus Ferment, Schisandra Chinensis Fruit Extract, Lycium Chinense Fruit Extract, Crataegus Oxyacantha Fruit Extract, Gardenia Jasminoides Fruit Extract, Cornus Officinalis Fruit Extract. May Contain: Iron Oxides (CI 77491, CI77492, CI 77499)

Questions or comments?

Visit www.purlisse.com or call weekdays at (424)777-0321.

Principal Display Panel - Perfect Glow BB Cream Sunscreen SPF 30 40 mL – Tan Deep

pūrlisse

Perfect Glow

BB

CREAM

SUNSCREEN

SPF 30

oil free

moisturizing

natural-looking coverage

matte meets glowy finish

for all skin types,

even sensitive

net wt. 1.4 fl. oz / 40 mL